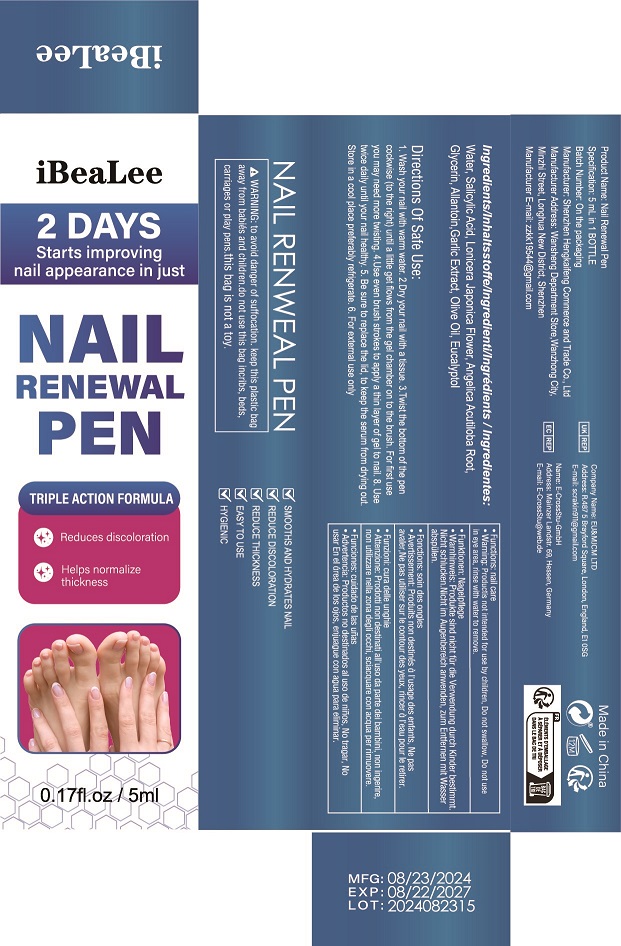 DRUG LABEL: Nail Renewal Pen
NDC: 84117-032 | Form: LIQUID
Manufacturer: Shenzhen Hengkaifeng Commerce and Trade Co., Ltd
Category: otc | Type: HUMAN OTC DRUG LABEL
Date: 20241017

ACTIVE INGREDIENTS: SALICYLIC ACID 1 g/100 mL
INACTIVE INGREDIENTS: WATER; OLIVE OIL

Active ingredients

Salicylic Acid

PURPOSE

Anti-fungal

Uses

Uses for relief and treatment of pain,soreness, and inflammation from nail fungus.
Symptoms: ■ discolored nails ■ brittle nails ■ distorted nails

Warnings

For external use only, Some individuals may be sensitive to essential oils.
Begin with a small drop to determine if product causes any irritation. Discontinue use if any irritation occurs.
Stop use and consult a doctor if condition worsens, Not for use on children under the age of 2 without physician direction.

Stop use and ask a doctor if

rash occur

Do not use

on damaged or broken skik

Keep out of reach of children.

If swallwed, get medical help or contact a Poison Control Center right away.

inactive ingredients

Water

DOSAGE & ADMINISTRATION

shake well before use.Wash and thoroughly dry the affectedarea. Apply 1-2 drops and gently rubinto affected area three times per day.